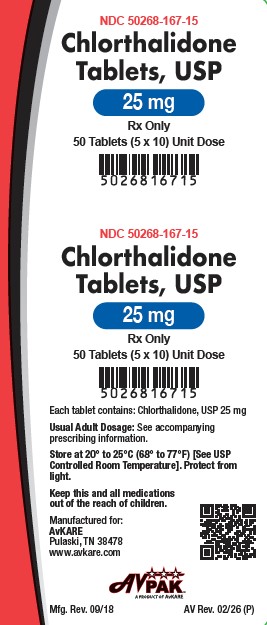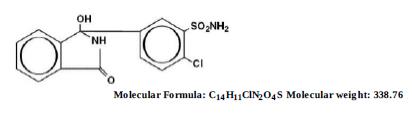 DRUG LABEL: CHLORTHALIDONE
NDC: 50268-167 | Form: TABLET
Manufacturer: AvPAK
Category: prescription | Type: HUMAN PRESCRIPTION DRUG LABEL
Date: 20260225

ACTIVE INGREDIENTS: CHLORTHALIDONE 25 mg/1 1
INACTIVE INGREDIENTS: SILICON DIOXIDE; MAGNESIUM STEARATE; CELLULOSE, MICROCRYSTALLINE; STARCH, CORN; SODIUM STARCH GLYCOLATE TYPE A CORN; TALC

CHLORTHALIDONE TABLETS, USP
Rx Only

DESCRIPTION

Chlorthalidone is an oral antihypertensive/diuretic. It is a monosulfamyl diuretic that differs chemically from thiazide diuretics in that a double-ring system is incorporated in its structure. It is 2-chloro-5(1- hydroxy-3-oxo-1-isoindolinyl) benzenesulfonamide with the following structural formula:

Chlorthalidone, USP is practically insoluble in water, in ether, and in chloroform; soluble in methanol; slightly soluble in ethanol.

Chlorthalidone tablets are available containing either 25 mg or 50 mg of chlorthalidone USP and the following inactive ingredients: Colloidal silicon dioxide, Magnesium Stearate, Microcrystalline Cellulose, Pregelatinized Starch, Sodium Starch Glycolate Type-A, Talc.

CLINICAL PHARMACOLOGY

Chlorthalidone is an oral diuretic with prolonged action (48–72 hours) and low toxicity. The major portion of the drug is excreted unchanged by the kidneys. The diuretic effect of the drug occurs in approximately 2.6 hours and continues for up to 72 hours. The mean half-life following a 50 to 200 mg dose is 40 hours. In the first order of absorption, the elimination half-life is 53 hours following a 50 mg dose, and 60 hours following a 100 mg dose. Approximately 75 percent of the drug is bound to plasma proteins, 58 percent of the drug being bound to albumin. This is caused by an increased affinity of the drug to erythrocyte carbonic anhydrase. Nonrenal routes of elimination have yet to be clarified. Data are not available regarding percentage of dose as unchanged drug and metabolites, concentration of the drug in body fluids, degree of uptake by a particular organ or in the fetus, or passage across the blood-brain barrier.

The drug produces copious diuresis with greatly increased excretion of sodium and chloride. At maximal therapeutic dosage, chlorthalidone is approximately equal in its diuretic effect to comparable maximal therapeutic doses of benzothiadiazine diuretics. The site of action appears to be the cortical diluting segment of the ascending limb of Henle's loop of the nephron.

INDICATIONS AND USAGE

Diuretics such as chlorthalidone are indicated in the management of hypertension either as the sole therapeutic agent or to enhance the effect of other antihypertensive drugs in the more severe forms of hypertension.

Chlorthalidone is indicated as adjunctive therapy in edema associated with congestive heart failure, hepatic cirrhosis, and corticosteroid and estrogen therapy.

Chlorthalidone has also been found useful in edema due to various forms of renal dysfunction, such as nephrotic syndrome, acute glomerulonephritis, and chronic renal failure.Chlorthalidone has also been found useful in edema due to various forms of renal dysfunction, such as nephrotic syndrome, acute glomerulonephritis, and chronic renal failure.

Usage in Pregnancy

The routine use of diuretics in an otherwise healthy woman is inappropriate and exposes mother and fetus to unnecessary hazard. Diuretics do not prevent development of toxemia of pregnancy, and there is no satisfactory evidence that they are useful in the treatment of developed toxemia. Edema during pregnancy may arise from pathologic causes or from the physiologic and mechanical consequences of pregnancy. Chlorthalidone is indicated in pregnancy when edema is due to pathologic causes, just as it is in the absence of pregnancy (however, see PRECAUTIONS, below). Dependent edema in pregnancy, resulting from restriction of venous return by the expanded uterus, is properly treated through elevation of the lower extremities and use of support hose; use of diuretics to lower intravascular volume in this case is illogical and unnecessary. There is hypervolemia during normal pregnancy that is harmful to neither the fetus nor the mother (in the absence of cardiovascular disease), but that is associated with edema, including generalized edema, in the majority of pregnant women. If this edema produces discomfort, increased recumbency will often provide relief. In rare instances, this edema may cause extreme discomfort that is not relieved by rest. In these cases, a short course of diuretics may provide relief and be appropriate.

CONTRAINDICATIONS

Anuria.

Known hypersensitivity to chlorthalidone or other sulfonamide-derived drugs.

WARNINGS

Chlorthalidone should be used with caution in severe renal disease. In patients with renal disease, chlorthalidone or related drugs may precipitate azotemia. Cumulative effects of the drug may develop in patients with impaired renal function.

Chlorthalidone should be used with caution in patients with impaired hepatic function or progressive liver disease, since minor alterations of fluid and electrolyte balance may precipitate hepatic coma.

Sensitivity reactions may occur in patients with a history of allergy or bronchial asthma.

The possibility of exacerbation or activation of systemic lupus erythematosus has been reported with thiazide diuretics, which are structurally related to chlorthalidone. However, systemic lupus erythematosus has not been reported following chlorthalidone administration.

PRECAUTIONS

General

Hypokalemia may develop with chlorthalidone as with any other diuretic, especially with brisk diuresis when severe cirrhosis is present or during concomitant use of corticosteroids or ACTH.

Interference with adequate oral electrolyte intake will also contribute to hypokalemia. Digitalis therapy may exaggerate metabolic effects of hypokalemia especially with reference to myocardial activity.

Any chloride deficit is generally mild and usually does not require specific treatment except under extraordinary circumstances (as in liver disease or renal disease). Dilutional hyponatremia may occur in edematous patients in hot weather, appropriate therapy is water restriction, rather than administration of salt except in rare instances when the hyponatremia is life threatening. In actual salt depletion, appropriate replacement is the therapy of choice.

Hyperuricemia may occur or frank gout may be precipitated in certain patients receiving chlorthalidone.

Thiazide-like diuretics have been shown to increase the urinary excretion of magnesium; this may result in hypomagnesemia.

The antihypertensive effects of the drug may be enhanced in the post-sympathectomy patient.

If progressive renal impairment becomes evident, as indicated by a rising nonprotein nitrogen or blood urea nitrogen, a careful reappraisal of therapy is necessary with consideration given to withholding or discontinuing diuretic therapy.If progressive renal impairment becomes evident, as indicated by a rising nonprotein nitrogen or blood urea nitrogen, a careful reappraisal of therapy is necessary with consideration given to withholding or discontinuing diuretic therapy.

Calcium excretion is decreased by thiazide-like drugs. Pathological changes in the parathyroid gland with hypercalcemia and hypophosphatemia have been observed in few patients on thiazide therapy. The common complications of hyperparathyroidism such as renal lithiasis, bone resorption and peptic ulceration have not been seen.

Information for Patients

Patients should inform their physician if they have: (1) had an allergic reaction to chlorthalidone or other diuretics or have asthma, (2) kidney disease, (3) liver disease, (4) gout, (5) systemic lupus erythematosus, or (6) been taking other drugs such as cortisone, digitalis, lithium carbonate, or drugs for diabetes.

Patients should be cautioned to contact their physician if they experience any of the following symptoms of potassium loss: excess thirst, tiredness, drowsiness, restlessness, muscle pains or cramps, nausea, vomiting, or increased heart rate or pulse.

Patients should also be cautioned that taking alcohol can increase the chance of dizziness occurring.

Laboratory Tests

Periodic determination of serum electrolytes to detect possible electrolyte imbalance should be performed at appropriate intervals.

All patients receiving chlorthalidone should be observed for clinical signs of fluid or electrolyte imbalance: namely, hyponatremia, hypochloremic alkalosis, and hypokalemia. Serum and urine electrolyte determinations are particularly important when the patient is vomiting excessively or receiving parenteral fluids.

Drug Interactions

Chlorthalidone may add to or potentiate the action of other antihypertensive drugs. Potentiation occurs with ganglionic peripheral adrenergic blocking drugs.

Medication such as digitalis may also influence serum electrolytes. Warning signs, irrespective of cause, are: dryness of mouth, thirst, weakness, lethargy, drowsiness, restlessness, muscle pains or cramps, muscular fatigue, hypotension, oliguria, tachycardia, and gastrointestinal disturbances such as nausea and vomiting.

Insulin requirements in diabetic patients may be increased, decreased, or unchanged. Higher dosage of oral hypoglycemic agents may be required. Latent diabetes mellitus may become manifest during chlorthalidone administration.

Chlorthalidone and related drugs may increase the responsiveness to tubocurarine.

Chlorthalidone and related drugs may decrease arterial responsiveness to norepinephrine. This diminution is not sufficient to preclude effectiveness of the pressor agent for therapeutic use.

Drug/Laboratory Test Interactions

Chlorthalidone and related drugs may decrease serum PBI levels without signs of thyroid disturbance.

Carcinogenesis , Mutagenesis , Impairment of Fertility

No information is available.

Pregnancy

Teratogenic Effects. Pregnancy Category B

Reproduction studies have been performed in the rat and the rabbit at doses up to 420 times the human dose and have revealed no evidence of harm to the fetus due to chlorthalidone. There are, however, no adequate and well-controlled studies in pregnant women. Because animal reproduction studies are not always predictive of human response, this drug should be used during pregnancy only if clearly needed.

Nonteratogenic Effects

Thiazides cross the placental barrier and appear in cord blood. The use of chlorthalidone and related drugs in pregnant women requires that the anticipated benefits of the drug be weighed against possible hazards to the fetus. These hazards include fetal or neonatal jaundice, thrombocytopenia, and possibly other adverse reactions that have occurred in the adult.Thiazides cross the placental barrier and appear in cord blood. The use of chlorthalidone and related drugs in pregnant women requires that the anticipated benefits of the drug be weighed against possible hazards to the fetus. These hazards include fetal or neonatal jaundice, thrombocytopenia, and possibly other adverse reactions that have occurred in the adult.

Nursing Mothers

Thiazides are excreted in human milk. Because of the potential for serious adverse reactions in nursing infants from chlorthalidone, a decision should be made whether to discontinue nursing or to discontinue the drug, taking into account the importance of the drug to the mother.

Pediatric Use

Safety and effectiveness in children have not been established.

ADVERSE REACTIONS

The following adverse reactions have been observed, but there is not enough systematic collection of data to support an estimate of their frequency.

Gastrointestinal System Reactions: anorexia, gastric irritation, nausea, vomiting, cramping, diarrhea, constipation, jaundice (intrahepatic cholestatic jaundice), pancreatitis.

Central Nervous System Reactions: dizziness, vertigo, paresthesias, headache, xanthopsia.

Hematologic Reactions: leukopenia, agranulocytosis, thrombocytopenia, aplastic anemia.

Dermatologic-Hypersensitivity Reactions: purpura, photosensitivity, rash, urticaria, necrotizing angiitis (vasculitis, cutaneous vasculitis), Lyell's syndrome (toxic epidermal necrolysis).

Cardiovascular Reactions: orthostatic hypotension may occur and may be aggravated by alcohol, barbiturates, or narcotics.

Other Adverse Reactions: hyperglycemia, glycosuria, hyperuricemia, muscle spasm, weakness, restlessness, impotence.

Whenever adverse reactions are moderate or severe, chlorthalidone dosage should be reduced or therapy withdrawn.

To report SUSPECTED ADVERSE REACTIONS contact AvKARE at 1-855-361-3993; email drugsafety@avkare.com; or FDA at 1-800-FDA-1088 or www.fda.gov/medwatch.

OVERDOSAGE

Symptoms of acute overdosage include nausea, weakness, dizziness, and disturbances of electrolyte balance. The oral LD of the drug in the mouse and the rat is more than 25,000 mg/kg body weight. The minimum lethal dose (MLD) in humans has not been established. There is no specific antidote, but gastric lavage is recommended, followed by supportive treatment. Where necessary, this may include intravenous dextrose-saline with potassium, administered with caution.

DOSAGE AND ADMINISTRATION

Therapy should be initiated with the lowest possible dose. This dose should be titrated according to individual patient response to gain maximal therapeutic benefit while maintaining lowest dosage possible. A single dose given in the morning with food is recommended; divided daily doses are unnecessary.

Hypertension

Initiation: Therapy, in most patients, should be initiated with a single daily dose of 25 mg. If the response is insufficient after a suitable trial, the dosage may be increased to a single daily dose of 50 mg. If additional control is required, the dosage of chlorthalidone may be increased to 100 mg once daily or a second antihypertensive drug (step 2 therapy) may be added. Dosage above 100 mg daily usually does not increase effectiveness. Increases in serum uric acid and decreases in serum potassium are dose-related over the 25 to 100 mg/day range.

Maintenance: Maintenance doses may be lower than initial doses and should be adjusted according to individual patient response. Effectiveness is well sustained during continued use.

Edema

Initiation: Adults, initially 50 to 100 mg daily, or 100 mg on alternate days. Some patients may require 150 to 200 mg at these intervals or up to 200 mg daily. Dosages above this level, however, do not usually produce a greater response.

Maintenance: Maintenance doses may often be lower than initial doses and should be adjusted according to individual patient response. Effectiveness is well sustained during continued use.

HOW SUPPLIED

Chlorthalidone Tablets, USP are available containing 25 mg or 50 mg of Chlorthalidone, USP.

The 25 mg tablets are white to off-white, round, tablet debossed with “AC 145” on one side and plain on other side. They are available as follows:

NDC 50268-167-15 (10 tablets per card, 5 cards per carton).

The 50 mg tablets are white to off-white, round, scored tablet debossed “AC” and “146” on one side separated by horizontal and plain on other side. They are available as follows:

Store at 20° to 25°C (68° to 77°F). [See USP for Controlled Room Temperature.]

Protect from light.

Dispensed in Unit Dose Package. For Institutional Use Only.

Dispense in a tight, light-resistant container as defined in the USP using a child-resistant closure.

ANIMAL PHARMACOLOGY

Biochemical studies in animals have suggested reasons for the prolonged effect of chlorthalidone.

Absorption from the gastrointestinal tract is slow due to its low solubility. After passage to the liver, some of the drug enters the general circulation, while some is excreted in the bile, to be reabsorbed later. In the general circulation, it is distributed widely to the tissue, but is taken up in highest concentrations by the kidneys, where amounts have been found 72 hours after ingestion, long after it has disappeared from other tissues. The drug is excreted unchanged in the urine.

Manufactured for:
AvKARE
Pulaski, TN 38478

Mfg Rev. 09/21
AV Rev. 02/26(P)

AvPAK